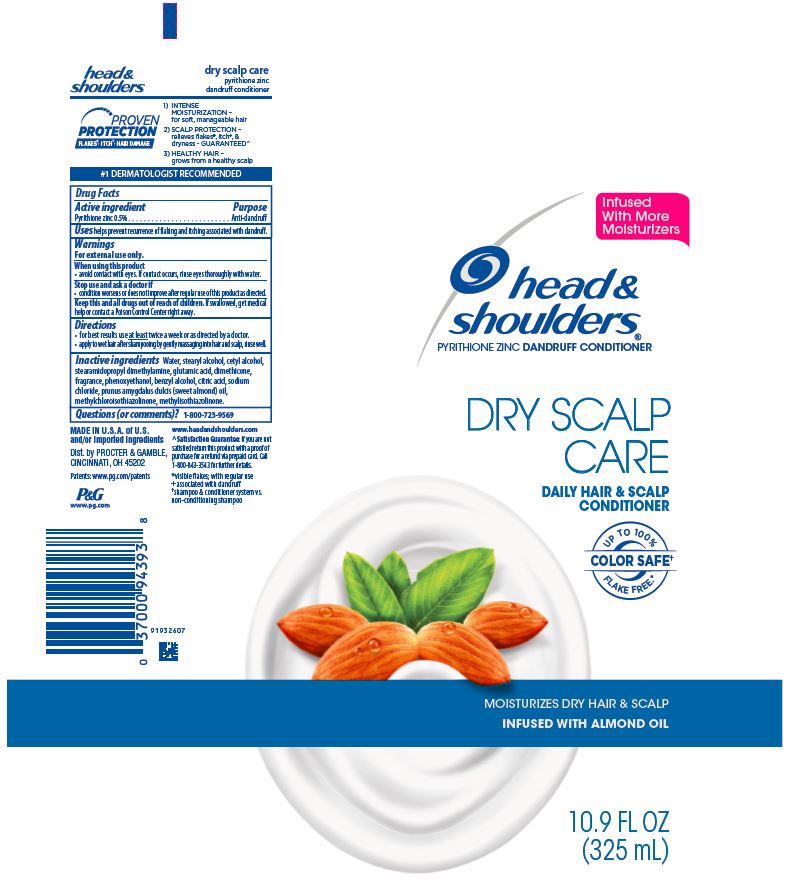 DRUG LABEL: Head and Shoulders Dry Scalp Care
NDC: 69423-160 | Form: LOTION
Manufacturer: The Procter & Gamble Manufacturing Company
Category: otc | Type: HUMAN OTC DRUG LABEL
Date: 20251218

ACTIVE INGREDIENTS: PYRITHIONE ZINC 0.5 g/100 mL
INACTIVE INGREDIENTS: WATER; STEARYL ALCOHOL; CETYL ALCOHOL; STEARAMIDOPROPYL DIMETHYLAMINE; GLUTAMIC ACID; DIMETHICONE; PHENOXYETHANOL; BENZYL ALCOHOL; CITRIC ACID MONOHYDRATE; SODIUM CHLORIDE; ALMOND OIL; METHYLCHLOROISOTHIAZOLINONE; METHYLISOTHIAZOLINONE

Head and Shoulders® Dry Scalp Care Hair and Conditioner

Drug Facts

Active ingredient

Pyrithione zinc 0.5%

Purpose

Anti-dandruff

Uses

helps prevent recurrence of flaking and itching associated with dandruff.

Warnings

For external use only.

When using this product

- avoid contact with eyes. If contact occurs, rinse eyes thoroughly with water.

Stop use and ask a doctor if

- condition worsens or does not improve after regular use of this product as directed.

KEEP OUT OF REACH OF CHILDREN

Keep this and all drugs out of reach of children. If swallowed, get medical help or contact a Poison Control Center right away.

Directions

- for best results use at least twice a week or as directed by a doctor.
- apply to wet hair after shampooing by gently massaging into hair and scalp, rinse well.

Inactive ingredients

Water, stearyl alcohol, cetyl alcohol, stearamidopropyl dimethylamine, glutamic acid, dimethicone, fragrance, phenoxyethanol, benzyl alcohol, citric acid, sodium chloride, prunus amygdalus dulcis (sweet almond) oil, methylchloroisothiazolinone, methylisothiazolinone.

Questions (or comments)?

1-800-723-9569

Dist. by PROCTER & GAMBLE,
CINCINNATI, OH 45202

PRINCIPAL DISPLAY PANEL - 325 mL Tube Label

head &
shoulders®
pyrithione zinc dandruff conditioner

dry scalp care

DAILY HAIR & SCALP

CONDITIONER

moisturizes dry hair & scalp

infused with almond oil

10.9 FL OZ (325 mL)